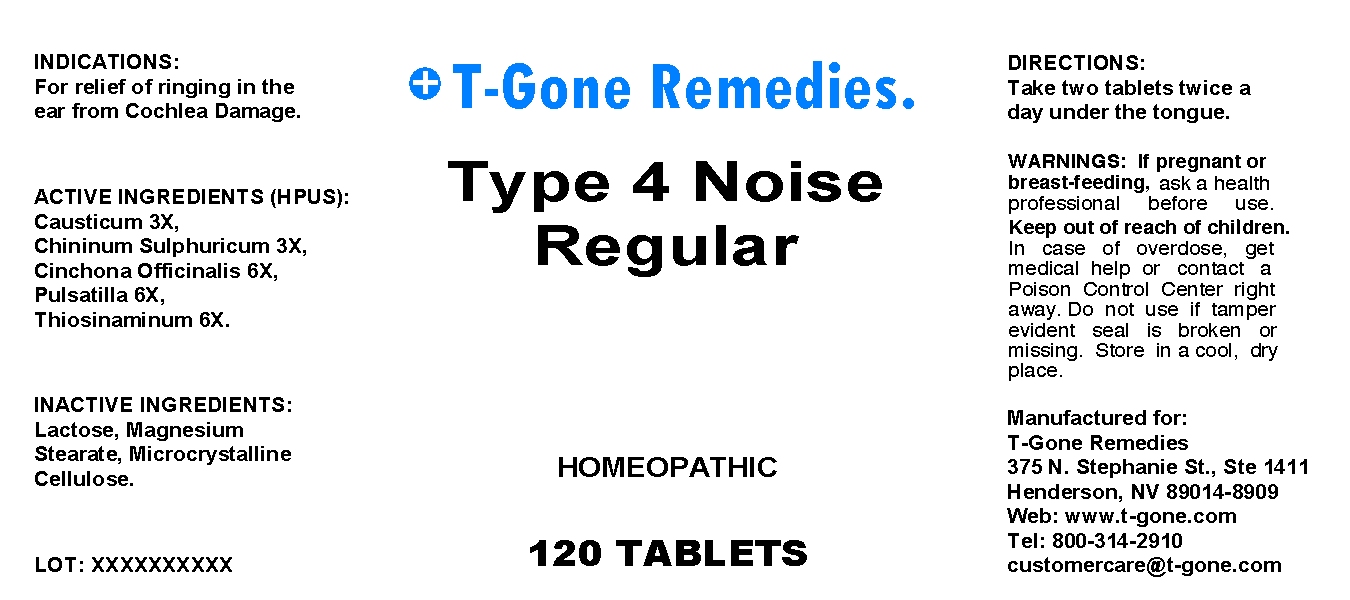 DRUG LABEL: Type 4 Noise Regular
NDC: 57520-0427 | Form: TABLET
Manufacturer: Apotheca Company
Category: homeopathic | Type: HUMAN OTC DRUG LABEL
Date: 20100715

ACTIVE INGREDIENTS: CAUSTICUM 3 [hp_X]/1 mg; QUININE SULFATE 3 [hp_X]/1 mg; CINCHONA OFFICINALIS BARK 6 [hp_X]/1 mg; PULSATILLA VULGARIS 6 [hp_X]/1 mg; ALLYLTHIOUREA 6 [hp_X]/1 mg
INACTIVE INGREDIENTS: LACTOSE; MAGNESIUM STEARATE; CELLULOSE, MICROCRYSTALLINE

Type 4 Noise Regular

ACTIVE INGREDIENT

ACTIVE INGREDIENTS: Causticum 3X, Chininum sulphuricum 3X, Cinchona officinalis 6X, Pulsatilla 6X, Thiosinaminum 6X.

PURPOSE

INDICATIONS: For relief of ringing in the ear from Cochlea Damage.

WARNINGS

WARNINGS: If pregnant or breast-feeding, ask a health professional before use.

Keep out of reach of children. In case of overdose, get medical help or contact a Poison Control Center right away.

Do not use if tamper evident seal is broken or missing. Store in a cool, dry place.

DOSAGE AND ADMINISTRATION

DIRECTIONS: Take two tablets twice a day under tongue.

INACTIVE INGREDIENT

INACTIVE INGREDIENTS: Lactose, Magnesium stearate, Microcrystalline cellulose.

QUESTIONS

Manufactured for:

T-Gone Remedies

375 N. Stephanie St., Ste 1411

Henderson, NV 59014-8909

Web: www.t-gone.com

Tel: 800-314-2910

customercare@t-gone.com

PACKAGE LABEL

T-Gone Remedies.

Type 4 Noise Regular

HOMEOPATHIC

120 TABLETS